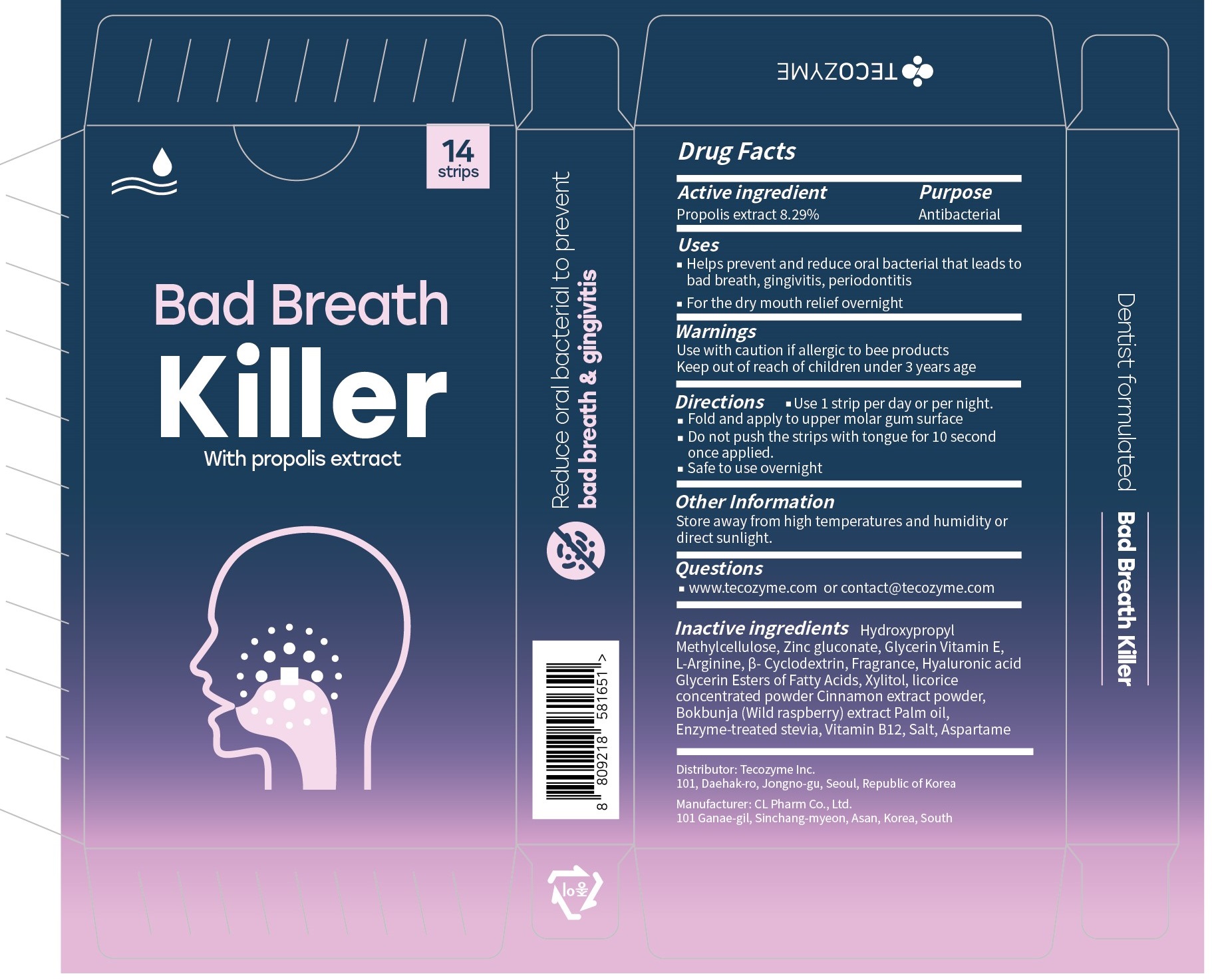 DRUG LABEL: Bad Breath Killer
NDC: 79717-0011 | Form: STRIP
Manufacturer: TECOZYME INC
Category: otc | Type: HUMAN OTC DRUG LABEL
Date: 20210817

ACTIVE INGREDIENTS: PROPOLIS WAX 8.29 mg/100 mg
INACTIVE INGREDIENTS: HYPROMELLOSE, UNSPECIFIED; Zinc gluconate; Xylitol

ACTIVE INGREDIENT

Propolis extract 8.29%

PURPOSE

Antibacterial

Uses

■ Helps prevent and reduce oral bacterial that leads to bad breath, gingivitis, periodontitis
■ For the dry mouth relief overnight

WARNINGS

Use with caution if allergic to bee products
Keep out of reach of children under 3 years age

Keep out of reach of children under 3 years age

Directions

■ Use 1 strip per day or per night.
■ Fold and apply to upper molar gum surface
■ Do not push the strips with tongue for 10 second once applied.
■ Safe to use overnight

Other Information

Store away from high temperatures and humidity or direct sunlight.

QUESTIONS

■ www.tecozyme.com or contact@tecozyme.com

INACTIVE INGREDIENTS

Hydroxypropyl Methylcellulose, Zinc gluconate, Glycerin Vitamin E, L-Arginine, β- Cyclodextrin, Fragrance, Hyaluronic acid, Glycerin Esters of Fatty Acids, Xylitol, licorice concentrated powder, Cinnamon extract powder, Bokbunja (Wild raspberry) extract, Palm oil, Enzyme-treated stevia, Vitamin B12, Salt, Aspartame